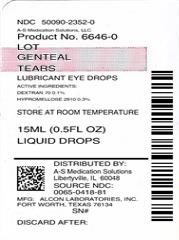 DRUG LABEL: GenTeal Tears (Mild) 
NDC: 50090-2352 | Form: SOLUTION/ DROPS
Manufacturer: A-S Medication Solutions
Category: otc | Type: HUMAN OTC DRUG LABEL
Date: 20200118

ACTIVE INGREDIENTS: DEXTRAN 70 1 mg/1 mL; HYPROMELLOSE 2910 (4000 MPA.S) 3 mg/1 mL
INACTIVE INGREDIENTS: Polidronium Chloride; Potassium Chloride; Water; Sodium Borate; Sodium Chloride; Hydrochloric Acid; Sodium Hydroxide

Drug Facts

ACTIVE INGREDIENT

Active Ingredients | Purpose
Dextran 70 0.1% | Lubricant
Hypromellose 2910 0.3% | Lubricant

Uses

- temporary relief of burning and irritation due to dryness of the eye
- temporary relief of discomfort due to minor irritations of the eye or to exposure to wind or sun
- as a protectant against further irritation

Warnings

For external use only

Do not use

- if solution changes color or becomes cloudy
- if you are sensitive to any ingredient in this product

When using this product

- to avoid contamination, do not touch tip of container to any surface
- replace cap after using

Stop use and ask a doctor if you experience any of the following:

- eye pain
- changes in vision
- continued redness or irritation of the eye
- condition worsens or persists for more than 72 hours

Keep out of reach of children.

If swallowed, get medical help or contact a Poison Control Center right away.

Directions

- put 1 or 2 drops in the affected eye(s) as needed

Other information

- store at room temperature

Inactive ingredients:

POLYQUAD* (polyquaternium-1) 0.001% preservative, potassium chloride, purified water, sodium borate and sodium chloride. May contain hydrochloric acid and/or sodium hydroxide to adjust pH.

HOW SUPPLIED

Product: 50090-2352

NDC: 50090-2352-0 15 mL in a BOTTLE, DROPPER / 1 in a CARTON

Questions?

In the U.S. call 1-800-757-9195
(Mon-Fri 9AM-5PM CST)
alcon.medinfo@alcon.com